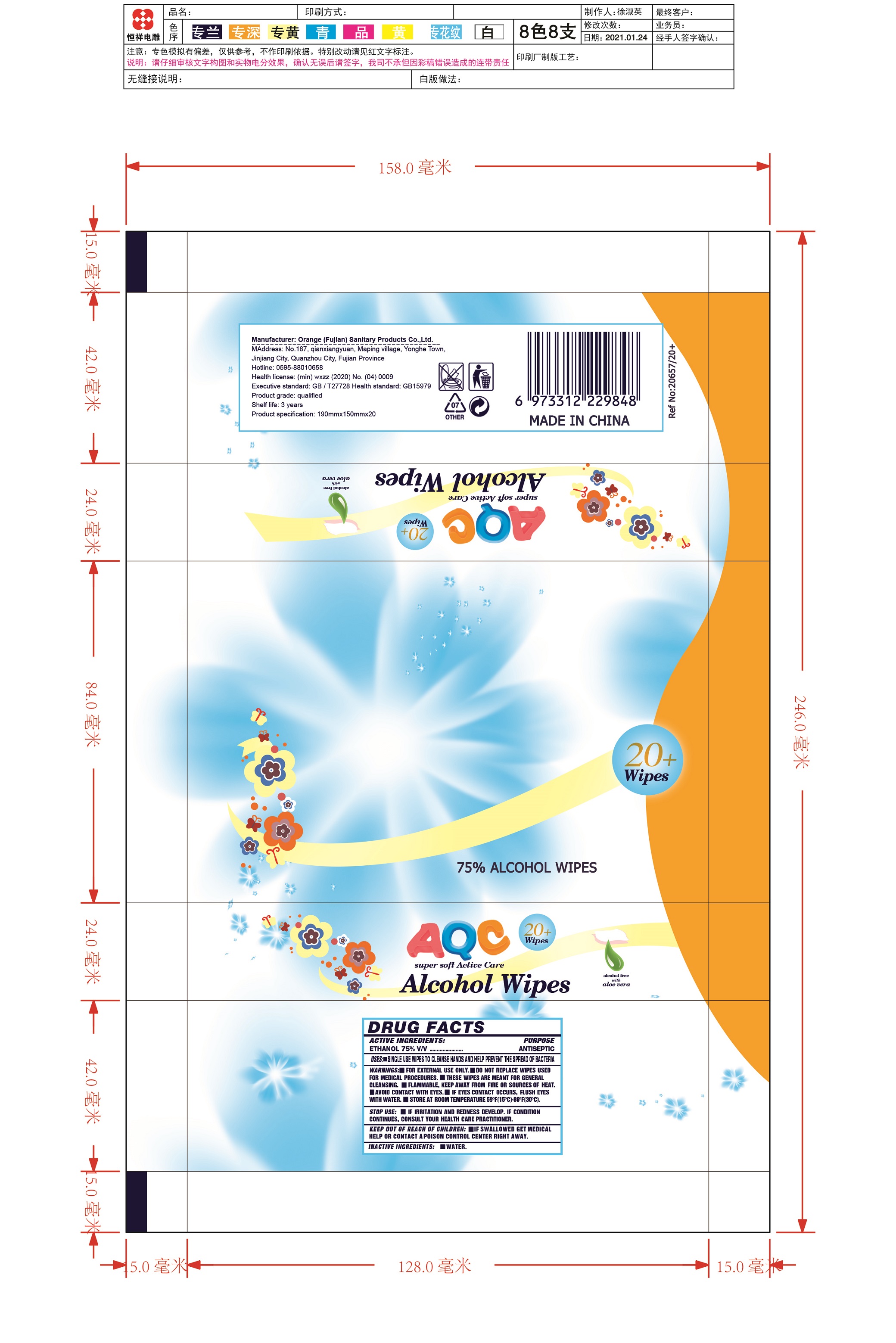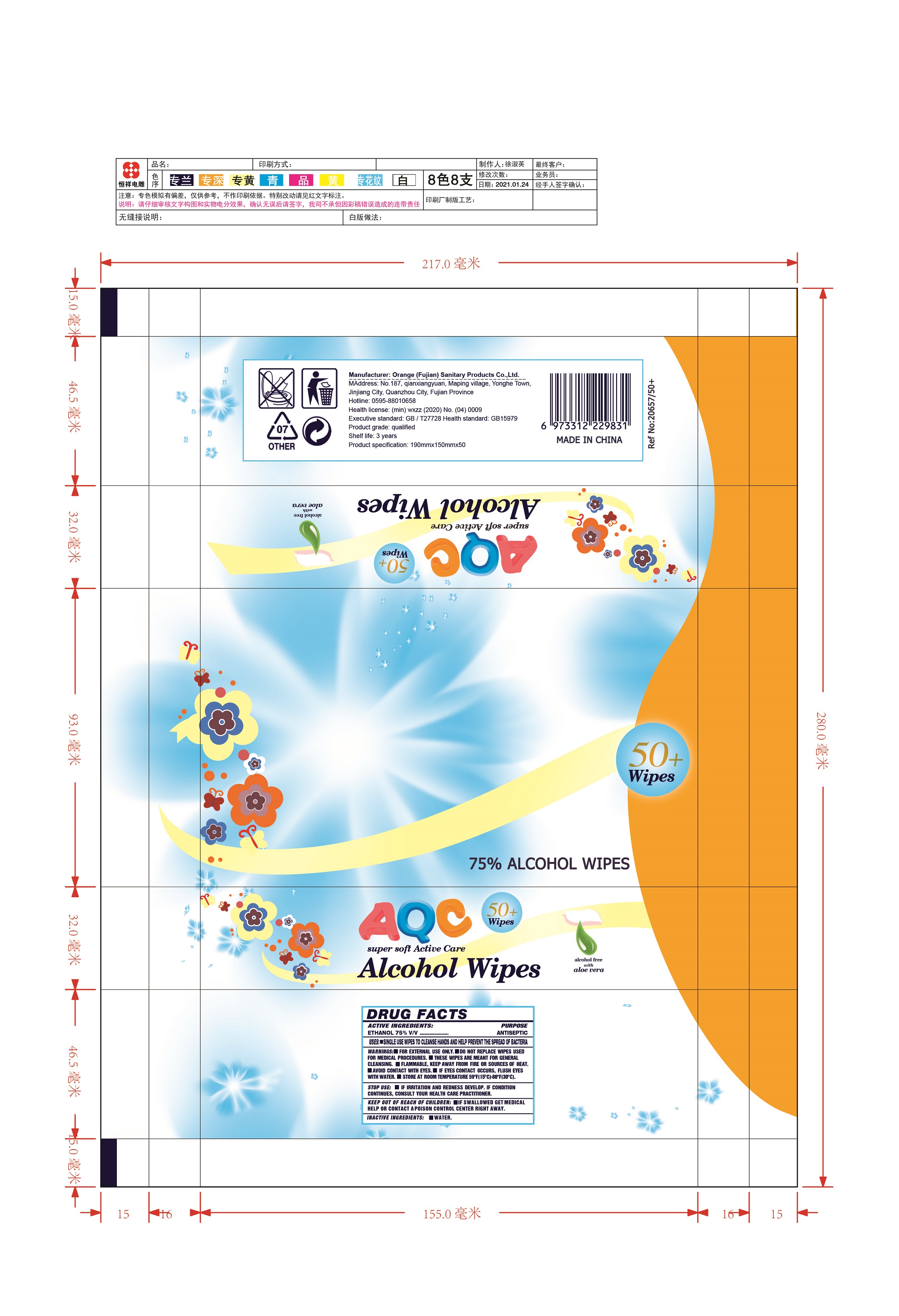 DRUG LABEL: 75% ALCOHOL WIPES
NDC: 81614-075 | Form: CLOTH
Manufacturer: Orange (Fujian) Sanitary Products Co., Ltd.
Category: otc | Type: HUMAN OTC DRUG LABEL
Date: 20210222

ACTIVE INGREDIENTS: ALCOHOL 75 mL/100 mL
INACTIVE INGREDIENTS: WATER

81614-075-20 81614-075-50 75% ALCOHOL WIPES

Active Ingredient(s)

ALCOHOL75% v/v. Purpose: Antiseptic

Purpose

Antiseptic, 75% ALCOHOL WIPES

Use

USES:Single use wipes to cleanse hands and help prevent the spread of bacteria.

Warnings

- For external use only.
- Do not replace wipes used for medical procedures.
- These wipes are meant for general cleansing.
- Flammable. Keep away fire or sources of heat.
- Avoid contact with eyes.
- If eyes contact occurs, flush eyes with water.
- Store at room temperature 59 ℉（15℃）-86 ℉（30℃）.

Do not use

- in children less than 2 months of age
- on open skin wounds

When using this product keep out of eyes, ears, and mouth. In case of contact with eyes, rinse eyes thoroughly with water.
Stop use and ask a doctor if irritation or rash occurs. These may be signs of a serious condition.
Keep out of reach of children. If swallowed, get medical help or contact a Poison Control Center right away.

STOP USE

If irritation and redness develop. If condition continues, consult your health care practitoner.

- Keep out of reach of children.
- If swallowed, get medical help or contact a Poison Control Center right away.

Directions

- Place enough product on hands to cover all surfaces. Rub hands together until dry.
- Supervise children under 6 years of age when using this product to avoid swallowing.

Other information

- Store between 15-30C (59-86F)
- Avoid freezing and excessive heat above 40C (104F)

Inactive ingredients

WATER

Package Label - Principal Display Panel

20 cloth NDC: 81614-075-20

50 cloth NDC: 81614-075-50